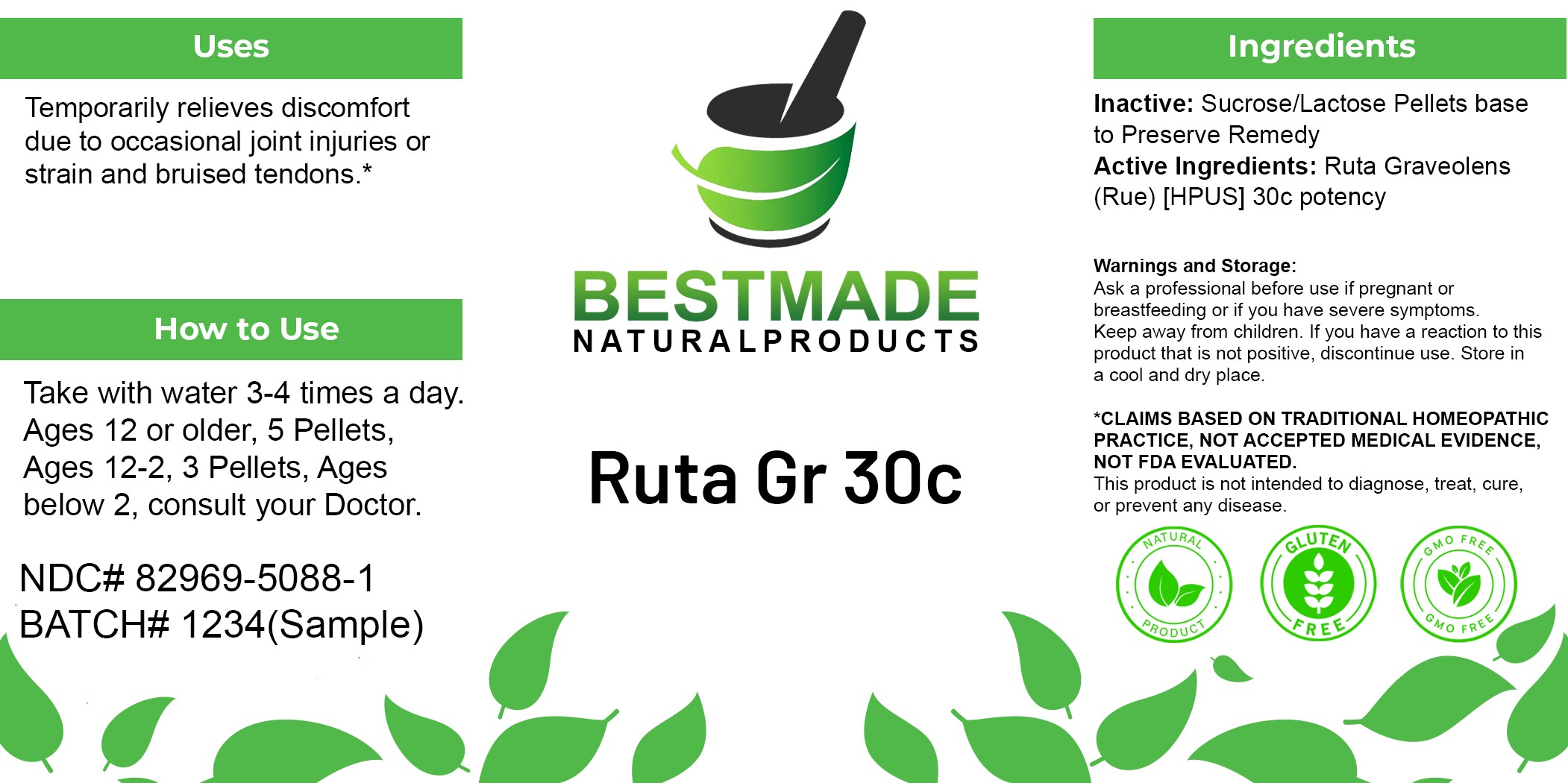 DRUG LABEL: Bestmade Natural Products Ruta Gr
NDC: 82969-5088 | Form: TABLET, SOLUBLE
Manufacturer: Bestmade Natural Products
Category: homeopathic | Type: HUMAN OTC DRUG LABEL
Date: 20250527

ACTIVE INGREDIENTS: RUTA GRAVEOLENS FLOWERING TOP 30 [hp_C]/30 [hp_C]
INACTIVE INGREDIENTS: SUCROSE 30 [hp_C]/30 [hp_C]; LACTOSE, UNSPECIFIED FORM 30 [hp_C]/30 [hp_C]

Ruta Graveolens 30c

DOSAGE AND ADMINISTRATION

How to Use

Take with water 3-4 times a day. Ages 12 or older, 5 Pellets, Ages 12-2, 3 Pellets, Ages below 2, consult your Doctor.

INDICATIONS AND USAGE

Best for

Temporarily relieves discomfort due to occasional joint injuries or strain and bruised tendons.*

INACTIVE INGREDIENT

Ingredients

Inactive: Sucrose/Lactose Pellets base to Preserve Remedy

Active Ingredients: Ruta Graveolens (Rue) [HPUS] 30c potency

Warnings:

Ask a professional before use if pregnant or breastfeeding or if you have severe symptoms.

Keep away from children. If you have a reaction to this product that is not positive, discontinue use. Store in a cool and dry place

*CLAIMS BASED ON TRADITIONAL HOMEOPATHIC PRACTICE, NOT ACCEPTED MEDICAL EVIDENCE NOT FDA EVALUATED.
This product is not intended to diagnose, treat, cure, or prevent any disease.

PURPOSE

Best for

Temporarily relieves discomfort due to occasional joint injuries or strain and bruised tendons.*

Warnings:

Ask a professional before use if pregnant or breastfeeding or if you have severe symptoms.

Keep away from children. If you have a reaction to this product that is not positive, discontinue use. Store in a cool and dry place

*CLAIMS BASED ON TRADITIONAL HOMEOPATHIC PRACTICE, NOT ACCEPTED MEDICAL EVIDENCE NOT FDA EVALUATED.
This product is not intended to diagnose, treat, cure, or prevent any disease.

Entire package label